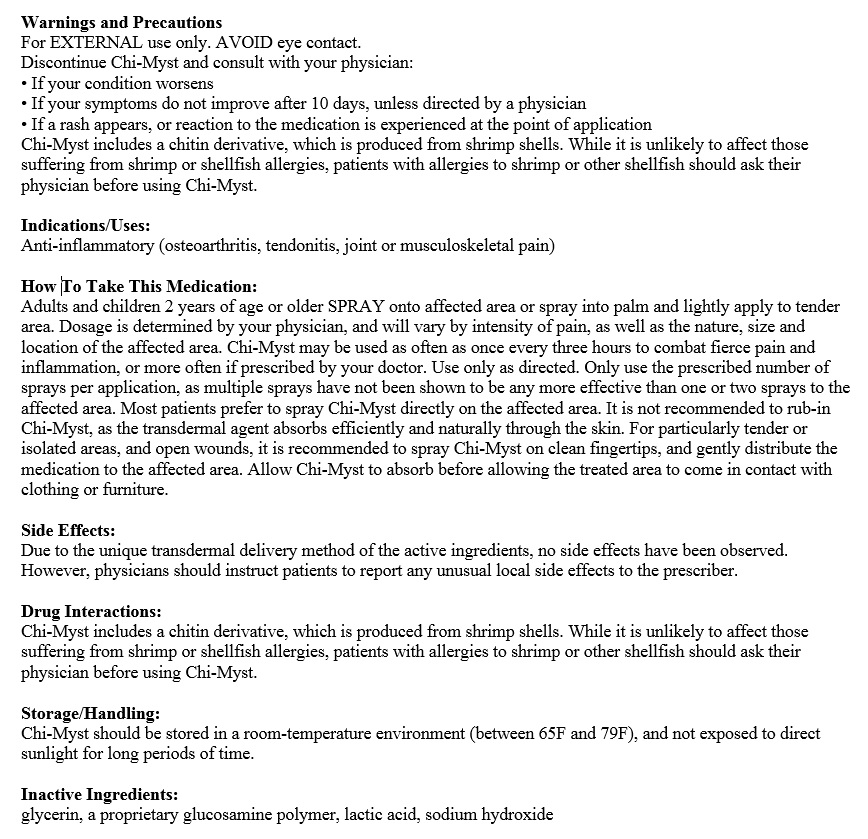 DRUG LABEL: Chi-Myst
NDC: 70486-001 | Form: SPRAY, METERED
Manufacturer: Prescription Care LLC
Category: prescription | Type: HUMAN PRESCRIPTION DRUG LABEL
Date: 20160819

ACTIVE INGREDIENTS: BUPIVACAINE HYDROCHLORIDE 0.3 g/100 mL; KETOROLAC TROMETHAMINE 0.3 g/100 mL; CHITOSAN LOW MOLECULAR WEIGHT (20-200 MPA.S) 0.1 g/100 mL
INACTIVE INGREDIENTS: GLYCERIN 0.3 mL/100 mL; WATER 100 mL/100 mL; LACTIC ACID LACTATE, DL- 0.14 mL/100 mL; SODIUM HYDROXIDE 0.045 g/100 mL

Chi-Myst Topical Spray